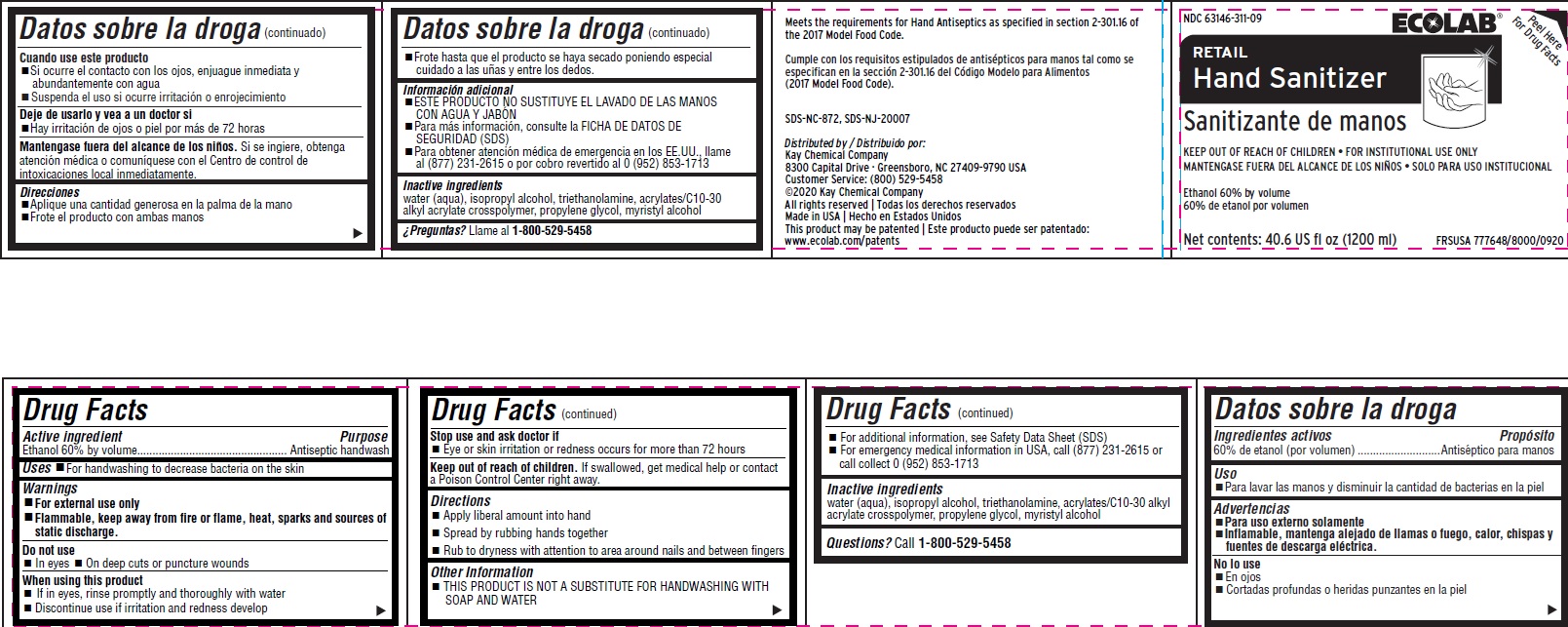 DRUG LABEL: Retail Hand Sanitizer
NDC: 47593-684 | Form: LIQUID
Manufacturer: Ecolab Inc.
Category: otc | Type: HUMAN OTC DRUG LABEL
Date: 20251230

ACTIVE INGREDIENTS: ALCOHOL 60 mL/100 mL
INACTIVE INGREDIENTS: WATER; ISOPROPYL ALCOHOL; TROLAMINE; CARBOMER COPOLYMER TYPE B (ALLYL PENTAERYTHRITOL CROSSLINKED); PROPYLENE GLYCOL; MYRISTYL ALCOHOL

Drug Facts

Active ingredient

Ethanol 60% by volume

Purpose

Antispetic handwash

Uses

- For handwashing to decrease bacteria on the skin

Warnings

- For external use only
- FLAMMABLE, keep away from fire or flame, heat, sparks and sources of static discharge

Do not use

- In eyes
- On deep cuts or puncture wounds

When using this product

- If in eyes, rinse promptly and thoroughly with water
- Discontinue use if irritation and rendess develop

Stop use and ask a doctor if

- Eye or skin irritation or redenss occurs for more than 72 hours

Keep out of reach of children. If swallowed, get medical help or contact a Poison Control Center right away.

Directions

- Apply liberal amount into hand
- Spread by rubbing hands together
- Rub to dryness with attention to are around nails and between fingers

Other information

- For additional information, see Safety Data Sheet (SDS)
- For emergency medical information in USA, call (877) 231-2615 or call collect 0 (952) 853-1713

INACTIVE INGREDIENT

Inactive ingredients water (aqua), isopropyl alcohol, triethanolamine, acrylates/C10-30 alkyl acrylate crosspolymer, propylene glycol, myristyl alcohol

Questions? Call 1-800-529-5458

Principal display panel and representative label

RETAIL

Hand Sanitizer

Sanitizante de manos

KEEP OUT OF REACH OF CHILDREN • FOR INSTITUTIONAL USE ONLY

MANTENGASE FUERA DEL ALCANCE DE LOS NIÑOS • SOLO PARA USO INSTITUCIONAL

Ethanol 60% by volume

60% de etanol por volume

Net contents: 40.6 US fl oz (1200 ml)

FRSUSA 777648/8000/0920

Meets the requirements for Hand Antiseptics as specified in section 2-301.16 of the 2017 Model Food Code.

Cumple con los requisitos estipulados de antisépticos para manos tal como se especifican en la sección 2-301.16 del Código Modelo para Alimentos

(2017 Model Food Code).

SDS-NC-872, SDS-NJ-20007

Distributed by / Distribuido por:

Kay Chemical Company

8300 Capital Drive · Greensboro, NC 27409-9790 USA

Customer Service: (800) 529-5458

©2020 Kay Chemical Company

All rights reserved | Todas los derechos reservados

Made in USA | Hecho en Estados Unidos

This product may be patented | Este producto puede ser patentado:

www.ecolab.com/patents